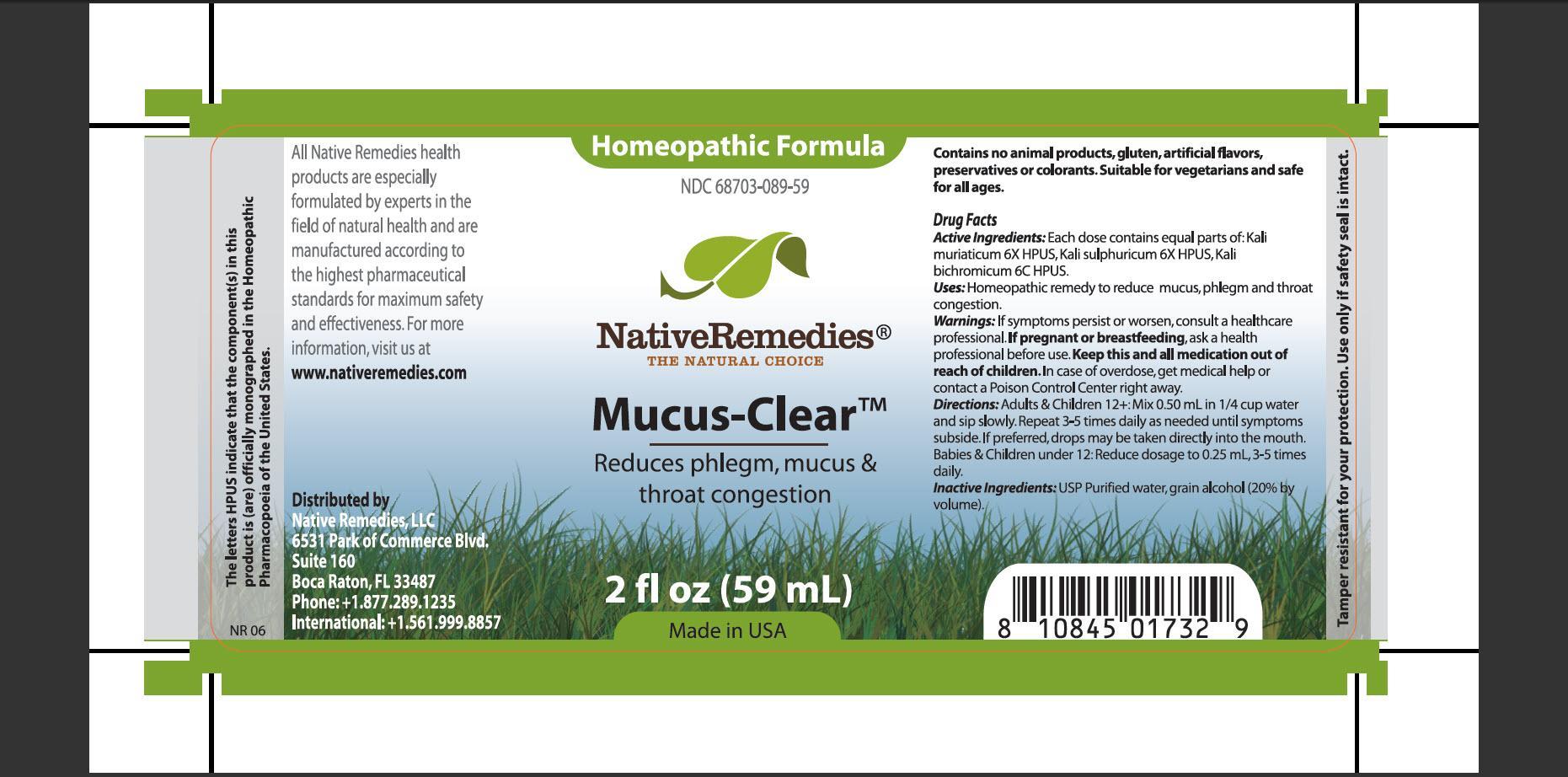 DRUG LABEL: Mucus-Clear
NDC: 68703-089 | Form: TINCTURE
Manufacturer: Native Remedies, LLC
Category: homeopathic | Type: HUMAN OTC DRUG LABEL
Date: 20130325

ACTIVE INGREDIENTS: POTASSIUM DICHROMATE 6 [hp_X]/1 mL; POTASSIUM CHLORIDE 6 [hp_X]/1 mL; POTASSIUM SULFATE 6 [hp_C]/1 mL
INACTIVE INGREDIENTS: WATER; ALCOHOL

Mucus-Clear

PURPOSE

Reduce phlegm, mucus and throat congestion

ACTIVE INGREDIENT

Active Ingredients:Each dose contains equal parts of: Kali muriaticum 6X HPUS, Kali sulphuricum 6X HPUS, Kali bichromicum 6C HPUS

INDICATIONS AND USAGE

Uses: Homeopathic remedy to reduce mucus, phlegm and throat congestion

WARNINGS

Warning: If symptoms persist or worsen, consult a healthcare professional

PREGNANCY OR BREAST FEEDING

If pregnant or breastfeeding, ask a health professional before use

KEEP OUT OF REACH OF CHILDREN

Keep this and all medication out of reach of children

OVERDOSAGE

In case of overdose, get medical help or contact a Poison Control Center right away

DOSAGE AND ADMINISTRATION

Directions: Adults and Children 12+: Mix 0.50 mL in 1/4 cup water and sip slowly. Repeat 3-5 times daily as needed until symptoms subside. If preferred, drops may be taken directly into the mouth. Babies and Children under 12 : Reduce dosage to 0.25 mL, 3-5 times daily

INACTIVE INGREDIENT

Inactive Ingredients:USP Purified water, grain alcohol (20% by volume).

PATIENT COUNSELING INFORMATION

The letters HPUS indicate that the components(s) in this product is (are) officially monographed in the Homeopathic Pharmacopoeia of the United States.

All Native Remedies health products are especially formulated by experts in the field of natural health and are manufactured according to the highest pharmaceutical standards for maximum safety and effectiveness. For more information, visit us at www.nativeremedies.com

Distributed by
Native Remedies, LLC
6531 Park of Commerce Blvd.
Suite 160
Boca Raton, FL 33487
Phone: +1.877.289.1235
International: +1.561.999.8857

Contains no animal products, gluten, artificial flavors, preservatives or colorants. Suitable for vegetarians and safe for all ages

STORAGE AND HANDLING

Tamper resistant for your protection. Use only if safety seal is intact